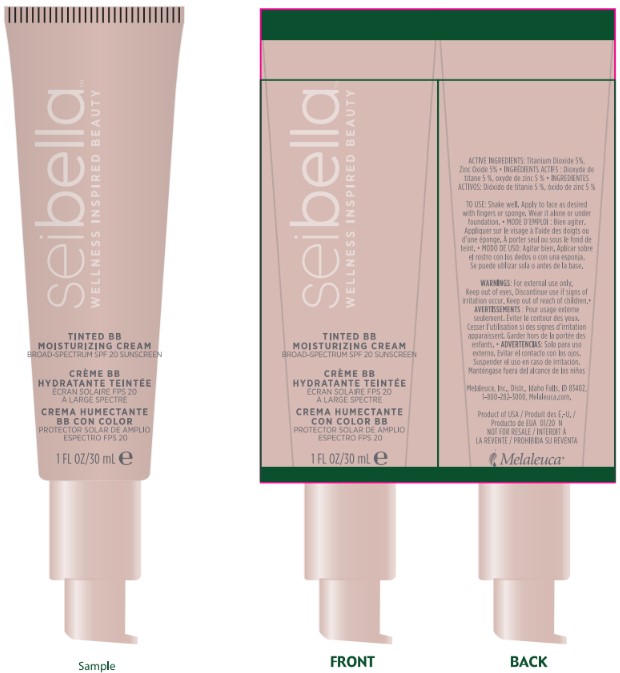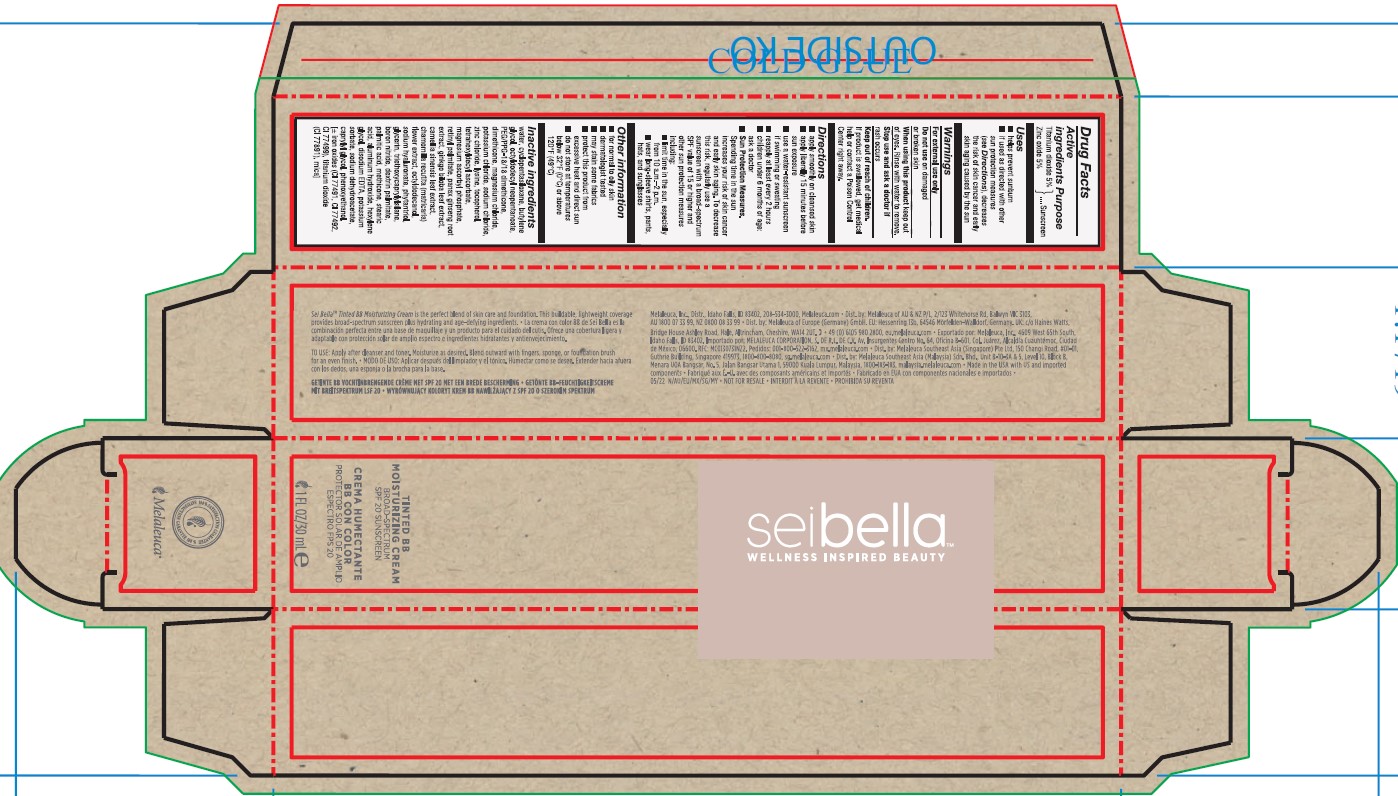 DRUG LABEL: Sei Bella Tinted BB Moisturizing Creme
NDC: 54473-284 | Form: LOTION
Manufacturer: Melaleuca Inc.
Category: otc | Type: HUMAN OTC DRUG LABEL
Date: 20251231

ACTIVE INGREDIENTS: TITANIUM DIOXIDE 1.5 g/30 mL; ZINC OXIDE 1.5 g/30 mL
INACTIVE INGREDIENTS: POTASSIUM SORBATE; PEG/PPG-18/18 DIMETHICONE; WATER; MAGNESIUM CHLORIDE; CAMELLIA OLEIFERA LEAF; TETRAHEXYLDECYL ASCORBATE; OCTYLDODECANOL; BORON NITRIDE; DEXTRIN PALMITATE (CORN; 20000 MW); STEARIC ACID; PANAX GINSENG ROOT OIL; MATRICARIA CHAMOMILLA FLOWERING TOP OIL; TRIETHOXYCAPRYLYLSILANE; ALUMINUM HYDROXIDE; GLYCERIN; HEXYLENE GLYCOL; BUTYLENE GLYCOL; OCTYLDODECYL NEOPENTANOATE; POTASSIUM CHLORIDE; SODIUM CHLORIDE; ZINC CHLORIDE; LYSINE; TOCOPHEROL; MAGNESIUM ASCORBYL PHOSPHATE; DIMETHICONE; GINKGO BILOBA LEAF OIL; PHYTANTRIOL; PALMITIC ACID; METHICONE (20 CST); SODIUM DEHYDROACETATE; CAPRYLYL GLYCOL; PHENOXYETHANOL

Sei Bella Tinted BB Moisturizing Creme Light to Medium 200 N

Active Ingredient

Titanium Dioxide 5%

Zinc Oxide 5%

Purpose

Sunscreen

Use

- helps prevent sunburn
- If used as directed with other sun protection measures (see Directions), decreases the risk of skin cancer and early skin aging caused by the sun.

Warnings

For external use only

Do not use on damaged or broken skin

When using this product keep out of eyes. Rinse with water to remove.

Stop use and ask a doctor if rash occurs

Keep out of reach of children.

If product is swallowed, get medical help or contact a Poison Control Center right away.

Directions

- apply smoothly on cleansed skin
- apply liberally 15 minutes before sun exposure
- use a water-resistant sunscreen if swimming or sweating
- reapply at least every 2 hours
- children under 6 months: ask a doctor
- Sun Protection Measures. Spending time in the sun increases you risk of skin cancer and early skin aging. To decrease this risk, regularly use a sunscreen with a broad-spectrum SPF value of 15 or higher and other sun protection measures including:
- limit time in the sun, especially from 10 a.m.-2 p.m.
- wear long-sleeve shirts, pants, hats, and sunglasses

Other information

- for normal to oily skin
- dermatologist tested
- may stain some fabrics

STORAGE AND HANDLING

- protect this product from excesssive heat and direct sun
- do not store at temperatures below 32°F (0°C) or above 120°F (49°C)

Inactive ingredients

Water (Aqua), Cyclopentasiloxane, Butylene Glycol, Octyldodecyl Neopentanoate, PEG/PPG-18/18 Dimethicone, Dimethicone, Magnesium Chloride, Potassium Chloride, Sodium Chloride, Zinc Chloride, Lysine, Tocopherol, Tetrahexyldecyl Ascorbate, Magnesium Ascorbyl Phosphate, Retinyl Palmitate, Camellia Oleifera Leaf Extract, Chamomilla Recutita (Matricaria) Flower Extract, Ginkgo Biloba Leaf Extract, Panax Ginseng Root Extract, Octyldodecanol, Sodium Hyaluronate, Phytantriol, Glycerin, Triethoxycaprylylsilane, Boron Nitride, Dextrin Palmitate, Palmitic Acid, Methicone, Stearic Acid, Aluminum Hydroxide, Hexylene Glycol, Disodium EDTA, Potassium Sorbate, Sodium Dehydroacetate, Caprylyl Glycol, Phenoxyethanol

May Contain (+/-): Mica, Titanium Dioxide (CI 77891), Iron Oxides (CI 77491, CI 77492, CI 77499)